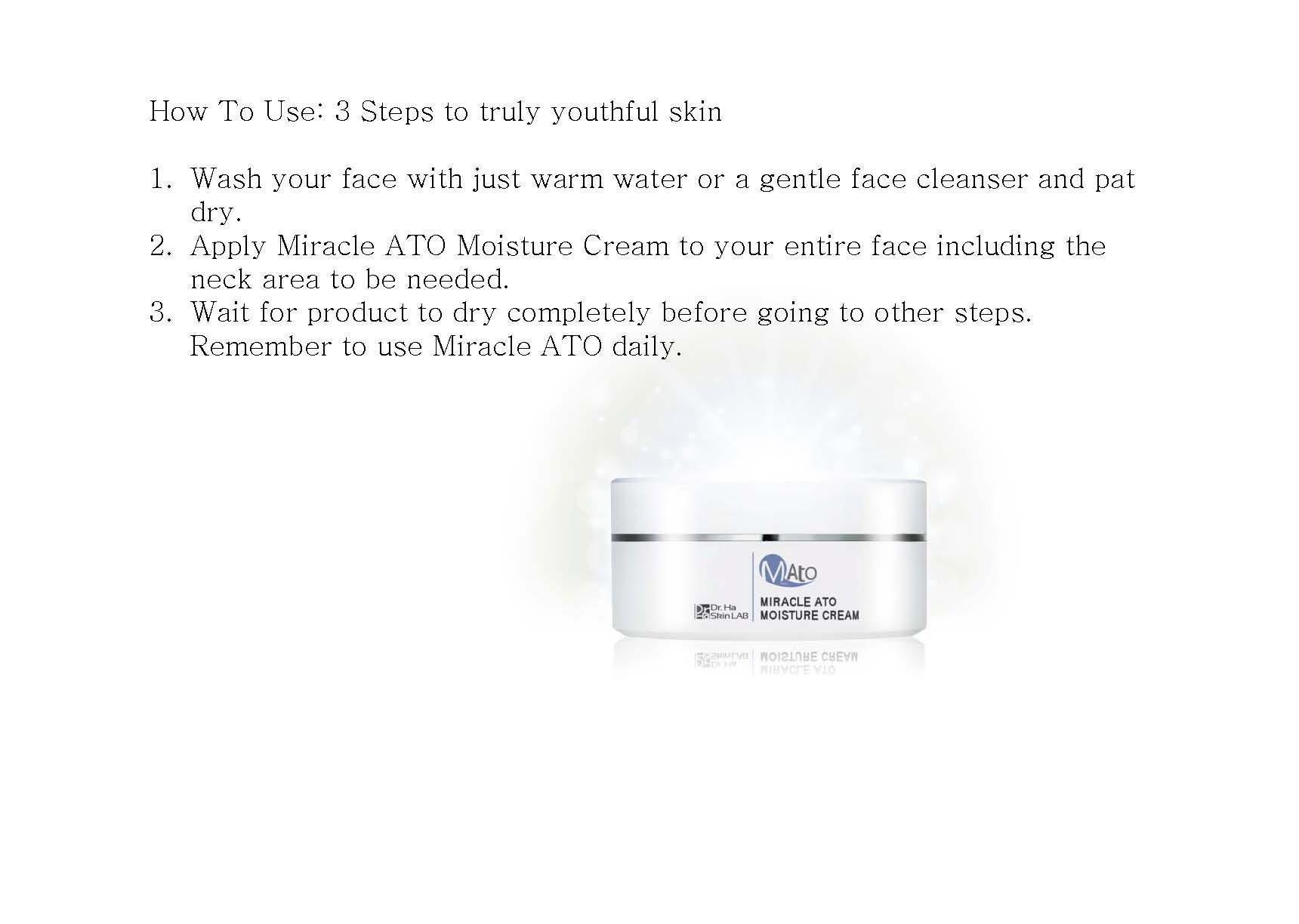 DRUG LABEL: MIRACLE ATO
                
NDC: 69309-1001 | Form: CREAM
Manufacturer: Dr. Ha Skin Lab Co.
Category: otc | Type: HUMAN OTC DRUG LABEL
Date: 20141022

ACTIVE INGREDIENTS: GLYCERIN 2 g/100 mL
INACTIVE INGREDIENTS: ADENOSINE; BUTYLENE GLYCOL

Drug Facts

ACTIVE INGREDIENT

glycerin

INACTIVE INGREDIENT

oriental herb ext, green tea ext, adenosine, water, butylene glycol etc

PURPOSE

for itching skin, lichenous skin trouble, skin balancing

keep out or reach of the children

INDICATIONS AND USAGE

Wash your face with just warm water or a gentle face cleanser and pat dry.
Apply Miracle ATO Moisture Cream to your entire face including the neck area to be needed.
Wait for product to dry completely before going to other steps. Remember to use Miracle ATO daily.

WARNINGS

- avoid direct sun exposure, keep it refrigerated or in cooler places
- do not eat

DOSAGE AND ADMINISTRATION

for exernal use only